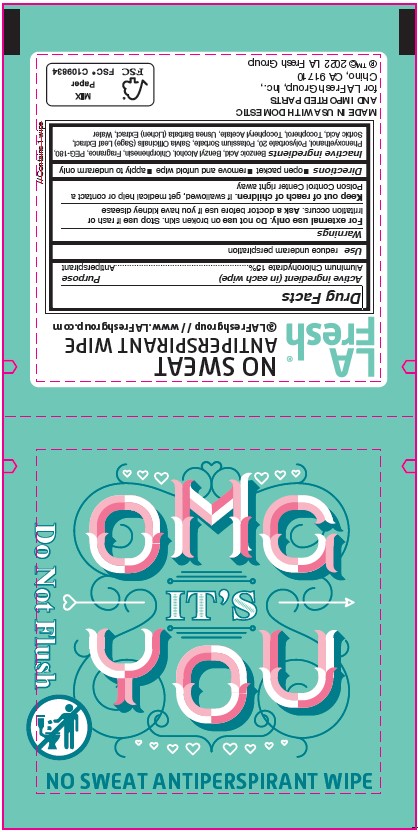 DRUG LABEL: LA FRESH Antiperspirant Wipe
NDC: 64709-160 | Form: CLOTH
Manufacturer: Diamond Wipes International, Inc
Category: otc | Type: HUMAN OTC DRUG LABEL
Date: 20250924

ACTIVE INGREDIENTS: ALUMINUM CHLOROHYDRATE 0.15 g/1 g
INACTIVE INGREDIENTS: USNEA BARBATA; TOCOPHEROL; CHLORPHENESIN; WATER; BENZOIC ACID; BENZYL ALCOHOL; POLYETHYLENE GLYCOL 8000; PHENOXYETHANOL; POTASSIUM SORBATE; POLYSORBATE 20; SAGE; SORBIC ACID; .ALPHA.-TOCOPHEROL ACETATE

LA FRESH Antiperspirant Wipe

Active ingredient

Aluminum Chlorohydrate 15%

Purpose

Antiperspirant

Use

reduce underarm perspiration

Warnings

For external use only

Do not use on broken skin

Stop use if rash or irritation occurs

Ask a doctor before use if you have kidney disease

Keep out of reach of children. If swallowed, get medical help or contact a Poison Control Center right away

Directions

■open packet ■remove and unfold wipe ■apply to underarm only

Inactive ingredients

Benzoic Acid, Benzyl Alcohol, Chlorphenesin, Fragrance, PEG-180, Phenoxyethanol, Polysorbate 20, Potassium Sorbate, Salvia Officinalis (Sage) Leaf Extract, Sorbic Acid, Tocopherol, Tocopheryl Acetate, Usnea Barbata (Lichen) Extract, Water

Label

OMG IT'S YOU

NO SWEAT ANTIPERSPIRANT WIPE

Do Not Flush

LA Fresh®

NO SWEAT ANTIPERSPIRANT WIPE
@LAFreshgroup // www.LAFreshgroup.com

Drug Facts
Active ingredient (in each wipe) Purpose
Aluminum Chlorohydrate 15%...................................Antiperspirant

Use reduce underam perspiration

Warnings
For external use only. Do not use on broken skin. Stop use if rash or

irritation occurs. Ask a doctor before use if you have kidney disease
Keep out of reach of children. If swallowed, get medical help or contact a
Poison Control Center right away

Directions ■open packet ■remove and unfold wipe ■apply to underarm only

Inactive ingredients Benzoic Acid, Benzyl Alcohol, Chlorphenesin, Fragrance, PEG-180, Phenoxyethanol, Polysorbate 20, Potassium Sorbate, Salvia Officinalis (Sage) Leaf Extract, Sorbic Acid, Tocopherol, Tocopheryl Acetate, Usnea Barbata (Lichen) Extract, Water

// Contains 1 wipe

MADE IN USA WITH DOMESTIC
AND IMPORTED PARTS
for LA Fresh Group, Inc.,
Chino, CA 91710
®™© 2022 LA Fresh Group

FSC MIX Paper FSC® C109834